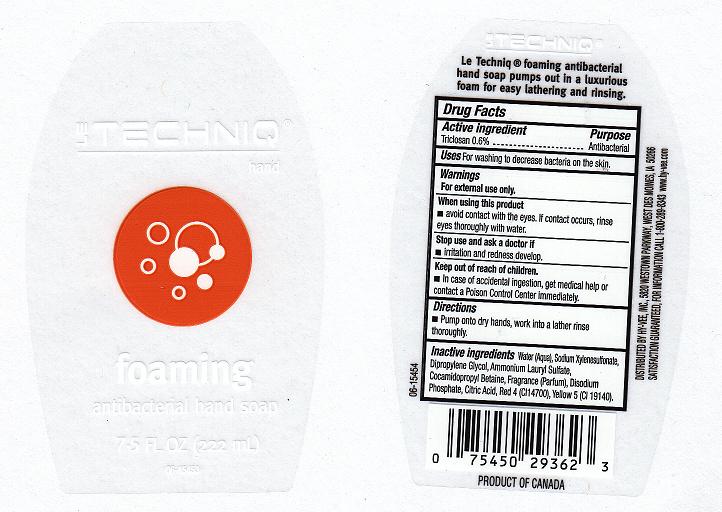 DRUG LABEL: FOAMING ANTIBACTERIAL
NDC: 42507-178 | Form: LIQUID
Manufacturer: HYVEE INC
Category: otc | Type: HUMAN OTC DRUG LABEL
Date: 20110609

ACTIVE INGREDIENTS: TRICLOSAN 0.46 mL/100 mL
INACTIVE INGREDIENTS: WATER; SODIUM  XYLENESULFONATE; DIPROPYLENE GLYCOL; GLYCERIN; AMMONIUM LAURYL SULFATE; COCAMIDOPROPYL BETAINE; SODIUM PHOSPHATE, DIBASIC, DIHYDRATE; CITRIC ACID MONOHYDRATE; FD&C RED NO. 4; FD&C YELLOW NO. 5

DRUG FACTS

Active Ingredient

Triclosan 0.6%

Purpose

Antibacterial

Uses

For hand washing to decrease bacteria on the skin.

Warnings

For external use only.

When using this product

Avoid contact with eyes. If contact occurs, rinse eyes thoroughly with water.

Stop using this product and ask doctor if

Irritation and redness develop.

Keep out of reach of children

In case of accidental ingestion, get medical help and contact Poison Control Center immediately.

Directions

Pump onto dry hands, work into a lather and rinse thoroughly.

INACTIVE INGREDIENTS

WATER, SODIUM XYLENE SULFONATE, DIPROPYLENE GLYCOL, GLYCERIN, AMMONIUM LAURYL SULFATE, COCAMIDOPROPYL BETAINE, FRAGRANCE, DISODIUM PHOSPHATE, CITRIC ACID, RED 4 (CI 14700), YELLOW 5 (CI 19140).